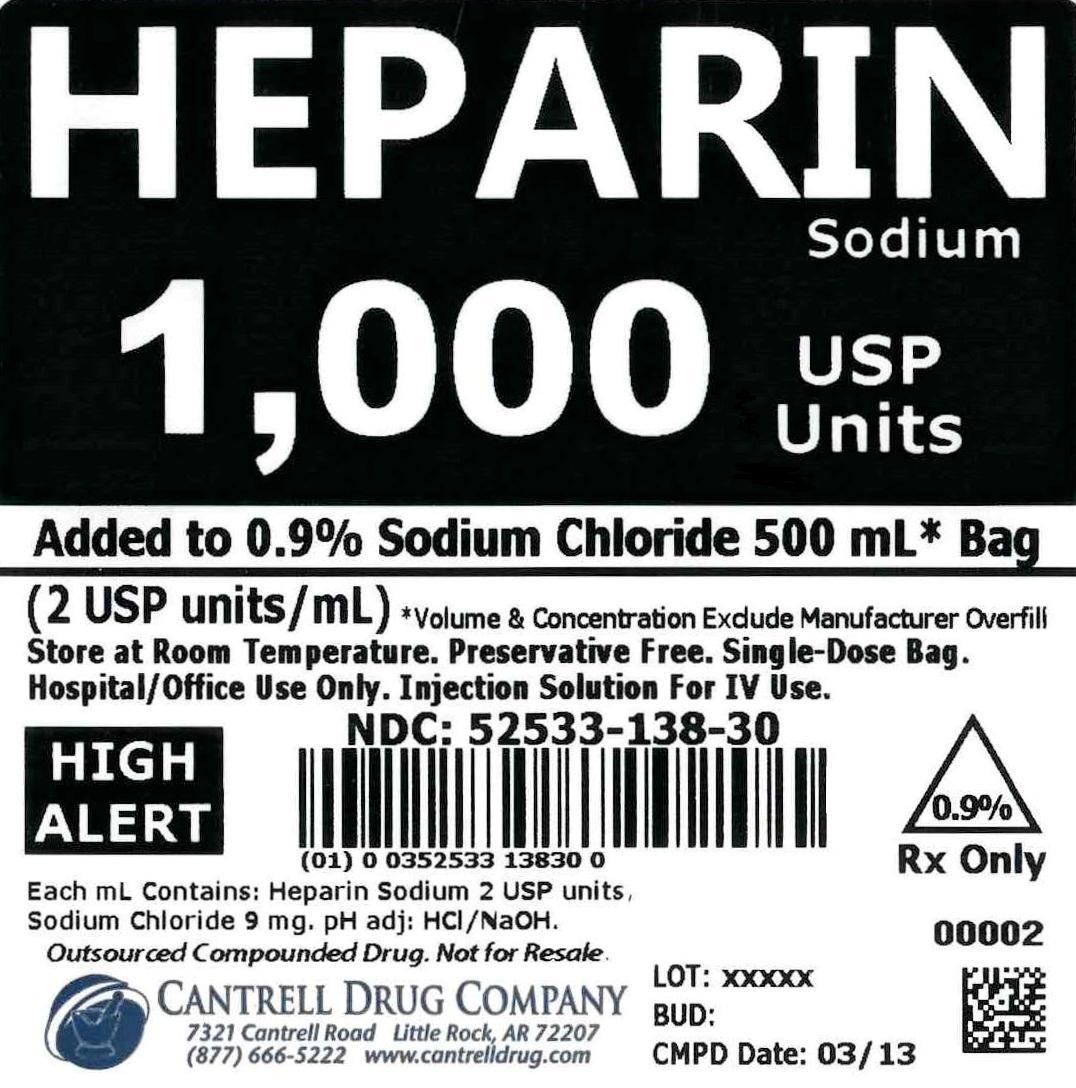 DRUG LABEL: Heparin Sodium
NDC: 52533-138 | Form: INJECTION, SOLUTION
Manufacturer: Cantrell Drug Company
Category: prescription | Type: HUMAN PRESCRIPTION DRUG LABEL
Date: 20141224

ACTIVE INGREDIENTS: Heparin Sodium 2 [USP'U]/1 mL
INACTIVE INGREDIENTS: SODIUM CHLORIDE 9 mg/1 mL; Water

Heparin Sodium 1,000 USP Units Added to 0.9% Sodium Chloride 500 mL Bag